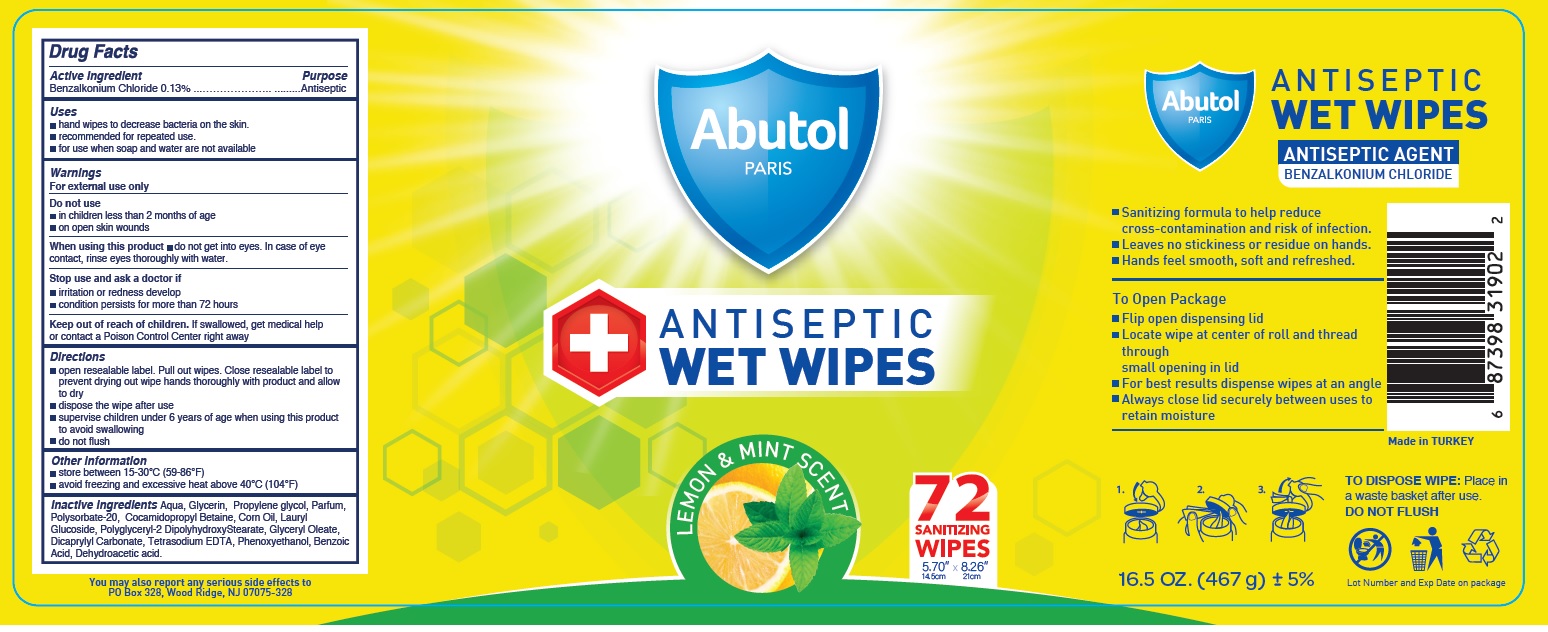 DRUG LABEL: Abutol ANTISEPTIC WET WIPES LEMON and MINT SCENT
NDC: 78089-038 | Form: CLOTH
Manufacturer: Endeks Kimya Sanayi Ve Ticaret Anonim Sirketi
Category: otc | Type: HUMAN OTC DRUG LABEL
Date: 20200829

ACTIVE INGREDIENTS: BENZALKONIUM CHLORIDE 0.13 g/100 g
INACTIVE INGREDIENTS: WATER; GLYCERIN; PROPYLENE GLYCOL; POLYSORBATE 20; COCAMIDOPROPYL BETAINE; CORN OIL; LAURYL GLUCOSIDE; POLYGLYCERYL-2 DIPOLYHYDROXYSTEARATE; GLYCERYL OLEATE; DICAPRYLYL CARBONATE; EDETATE SODIUM; PHENOXYETHANOL; BENZOIC ACID; DEHYDROACETIC ACID

Abutol ANTISEPTIC WET WIPES LEMON & MINT SCENT

Active Ingredient

Benzalkonium Chloride 0.13%

Purpose

Antiseptic

Uses

- hand wipes to decrease bacteria on the skin.
- recommended for repeated use.
- for use when soap and water are not available

Warnings

For external use only

Do not use

- in children less than 2 months of age
- on open skin wounds

When using this product • do not get into eyes. In case of eye contact, rinse eyes thoroughly with water.

Stop use and ask a doctor if

- irritation or redness develop
- condition persists for more than 72 hours

Keep out of reach of children. If swallowed, get medical help or contact a Poison Control Center right away

Directions

- open resealable label. Pull out wipes. Close resealable label to prevent drying out wipe hands thoroughly with product and allow to dry
- dispose the wipe after use
- supervise children under 6 years of age when using this product to avoid swallowing
- do not flush

Other information

- store between 15-30°C (59-86°F)
- avoid freezing and excessive heat above 40°C (104°F)

Inactive ingredients

Aqua, Glycerin, Propylene glycol, Parfum, Polysorbate-20, Cocamidopropyl Betaine, Corn Oil, Lauryl Glucoside, Polyglyceryl-2 DipolyhydroxyStearate, Glyceryl Oleate, Dicaprylyl Carbonate, Tetrasodium EDTA, Phenoxyethanol, Benzoic Acid, Dehydroacetic acid.

PARIS

LEMON & MINT SCENT

SANITIZING WIPES

You may also report any serious side effects to
PO Box 328, Wood Ridge, NJ 07075-328

ANTISEPTIC AGENT

- Sanitizing formula to help reduce cross-contamination and risk of infection.
- Leaves no stickiness or residue on hands.
- Hands feel smooth, soft and refreshed.

To Open Package

- Flip open dispensing lid
- Locate wipe at center of roll and thread through small opening in lid
- For best results dispense wipes at an angle
- Always close lid securely between uses to retain moisture

Made in TURKEY

TO DISPOSE WIPE: Place in a waste basket after use.
DO NOT FLUSH

Lot Number and Exp Date on package